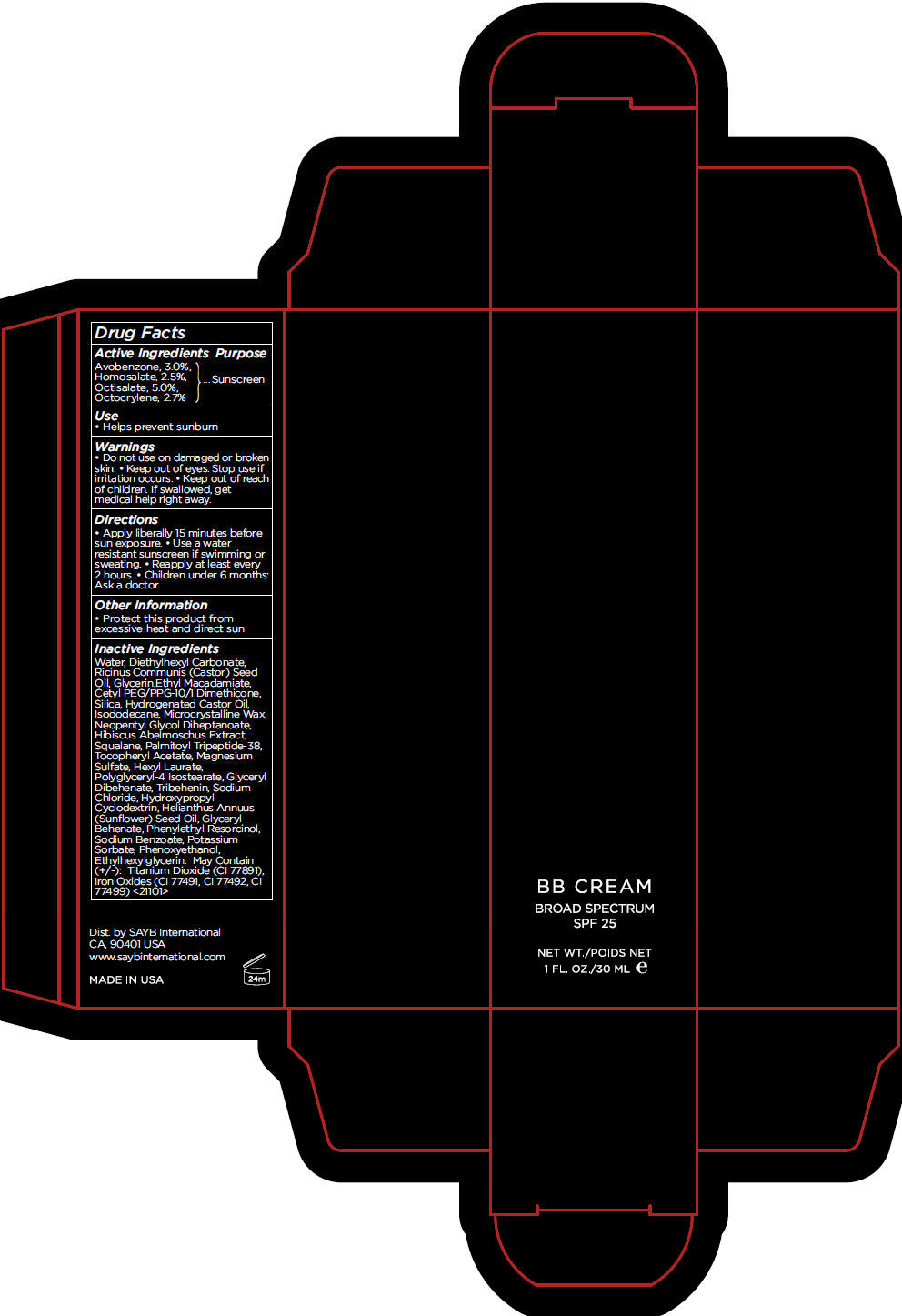 DRUG LABEL: BB FAIR
NDC: 56001-400 | Form: CREAM, AUGMENTED
Manufacturer: SAYB International
Category: otc | Type: HUMAN OTC DRUG LABEL
Date: 20151029

ACTIVE INGREDIENTS: Avobenzone 30 mg/1 mL; Homosalate 25 mg/1 mL; Octisalate 50 mg/1 mL; Octocrylene 27 mg/1 mL
INACTIVE INGREDIENTS: Water; Diethylhexyl Carbonate; Castor Oil; Glycerin; Ethyl Macadamiate; Cetyl PEG/PPG-10/1 Dimethicone (HLB 2); Silicon Dioxide; Hydrogenated Castor Oil; Isododecane; Microcrystalline Wax; Neopentyl Glycol Diheptanoate; Abelmoschus Moschatus Seed; Squalane; Palmitoyl Lysyldioxymethionyllysine; .Alpha.-Tocopherol Acetate; Magnesium Sulfate; Hexyl Laurate; Polyglyceryl-4 Isostearate; Glyceryl Dibehenate; Tribehenin; Sodium Chloride; Hydroxypropyl .Beta.-Cyclodextrin; Sunflower Oil; Phenylethyl Resorcinol; Sodium Benzoate; Potassium Sorbate; Phenoxyethanol; Ethylhexylglycerin; Titanium Dioxide; Ferric Oxide Yellow; Ferric Oxide Red; Ferrosoferric Oxide

BB Cream

Drug Facts

Active Ingredients

Avobenzone, 3.0%,
Homosalate, 2.5%,
Octisalate, 5.0%,
Octocrylene, 2.7%

Purpose

Sunscreen

Use

- Helps prevent sunburn

Warnings

- Do not use on damaged or broken skin.

STOP USE

- Keep out of eyes. Stop use if irritation occurs.

- Keep out of reach of children. If swallowed, get medical help right away.

Directions

- Apply liberally 15 minutes before sun exposure.
- Use a water resistant sunscreen if swimming or sweating.
- Reapply at least every 2 hours.
- Children under 6 months: Ask a doctor

Other Information

- Protect this product from excessive heat and direct sun

Inactive Ingredients

Water, Diethylhexyl Carbonate, Ricinus Communis (Castor) Seed Oil, Glycerin,Ethyl Macadamiate, Cetyl PEG/PPG-10/1 Dimethicone, Silica, Hydrogenated Castor Oil, Isododecane, Microcrystalline Wax, Neopentyl Glycol Diheptanoate, Hibiscus Abelmoschus Extract, Squalane, Palmitoyl Tripeptide-38, Tocopheryl Acetate, Magnesium Sulfate, Hexyl Laurate, Polyglyceryl-4 Isostearate, Glyceryl Dibehenate, Tribehenin, Sodium Chloride, Hydroxypropyl Cyclodextrin, Helianthus Annuus (Sunflower) Seed Oil, Glyceryl Behenate, Phenylethyl Resorcinol, Sodium Benzoate, Potassium Sorbate, Phenoxyethanol, Ethylhexylglycerin. May Contain (+/-): Titanium Dioxide (CI 77891), Iron Oxides (CI 77491, CI 77492, CI 77499) <21101>

Dist. by SAYB International
CA, 90401 USA

PRINCIPAL DISPLAY PANEL - 30 mL Tube Carton - FAIR

BB CREAM

BROAD SPECTRUM
SPF 25

NET WT.
1 FL. OZ./30 ML e

PRINCIPAL DISPLAY PANEL - 30 mL Tube Carton - LIGHT

BB CREAM

BROAD SPECTRUM
SPF 25

NET WT.
1 FL. OZ./30 ML e

PRINCIPAL DISPLAY PANEL - 30 mL Tube Carton - MEDIUM

BB CREAM

BROAD SPECTRUM
SPF 25

NET WT.
1 FL. OZ./30 ML e

PRINCIPAL DISPLAY PANEL - 30 mL Tube Carton - DARK

BB CREAM

BROAD SPECTRUM
SPF 25

NET WT.
1 FL. OZ./30 ML e